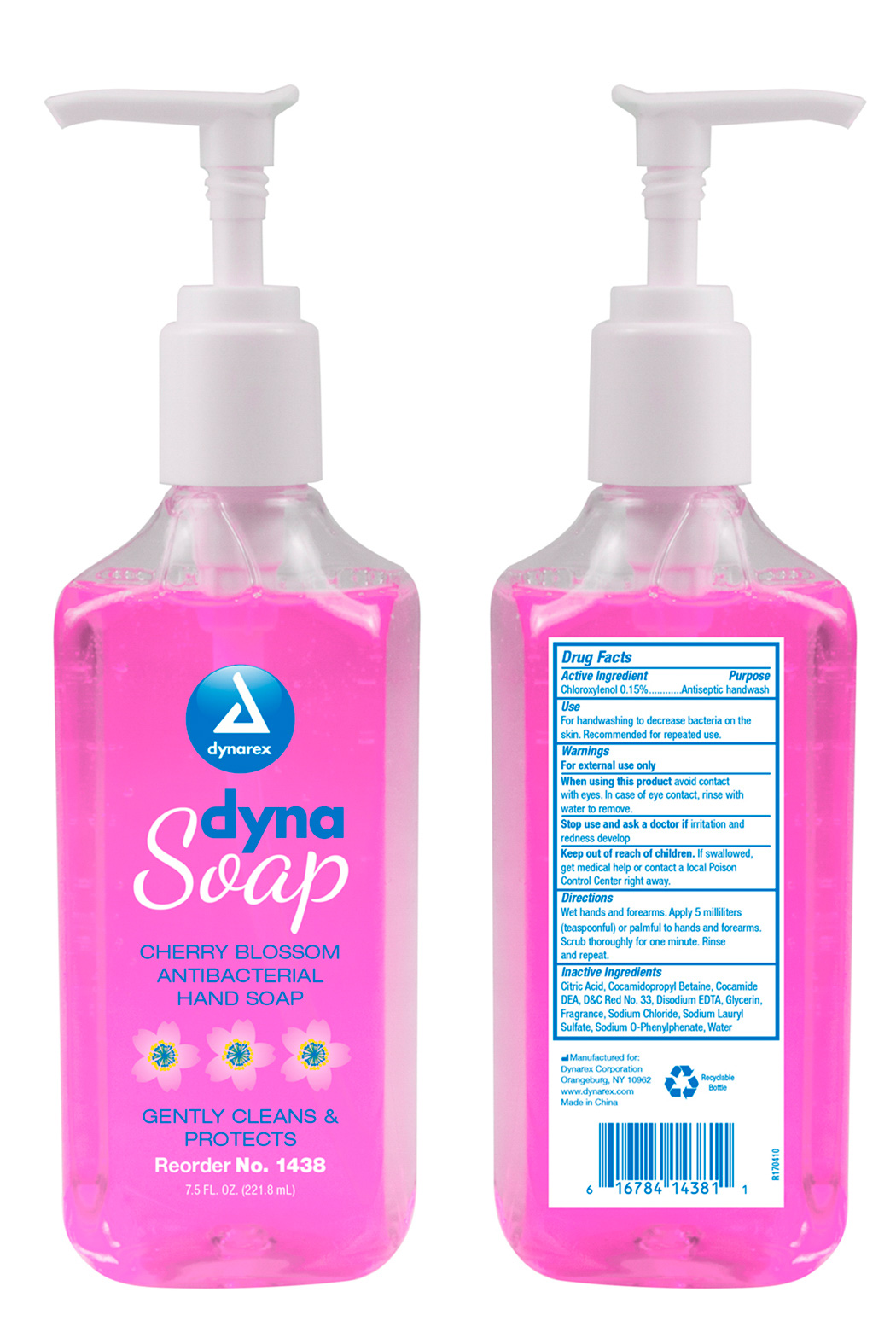 DRUG LABEL: Dynarex Green
NDC: 67777-318 | Form: LIQUID
Manufacturer: Dynarex Corporation
Category: otc | Type: HUMAN OTC DRUG LABEL
Date: 20241120

ACTIVE INGREDIENTS: CHLOROXYLENOL 0.15 g/100 mL
INACTIVE INGREDIENTS: ANHYDROUS CITRIC ACID; COCAMIDOPROPYL BETAINE; COCO DIETHANOLAMIDE; EDETATE DISODIUM; GLYCERIN; SODIUM LAURETH SULFATE; SODIUM CHLORIDE; WATER; SODIUM O-PHENYLPHENATE; D&C RED NO. 33

1438 Dynarex Antibacterial Hand Soap NDC 67777-318-01

ACTIVE INGREDIENT

Active Ingredient Purpose

Chloroxylenol 0.15% Antiseptic

WARNINGS

- For external use only
- When using this product avoid contact with eyes. In case of contact, flush with water.

PURPOSE

An antiseptic handwash.

Stop use and ask a doctor if irritation and redness develop.

INDICATIONS & USAGE

Cleaning and antiseptic cleansing of hands and skin.

DOSAGE & ADMINISTRATION

- Wet hands and forearms. Apply 5 milliliters (teaspoon) or palmful to hands and forearms. Scrub thoroughly for 1 minute. Rinse and repeat.

KEEP OUT OF REACH OF CHILDREN, if swallowed get medical help or contact a Poison Control Center right away.

INACTIVE INGREDIENTS

Inactive ingredients: Citric acid, Cocamidopropyl betaine, Cocmide DEA, D&C Red #33, Disodium EDTA, Frgarance, Glycerin, Sodium chloride, Sodium Lauryl Sulphate, Sodium o-phenylphenate, water.

PRINCIPAL DISPLAY PANEL

Dynarex Antibacterial Soap

1438 Soap.jpg